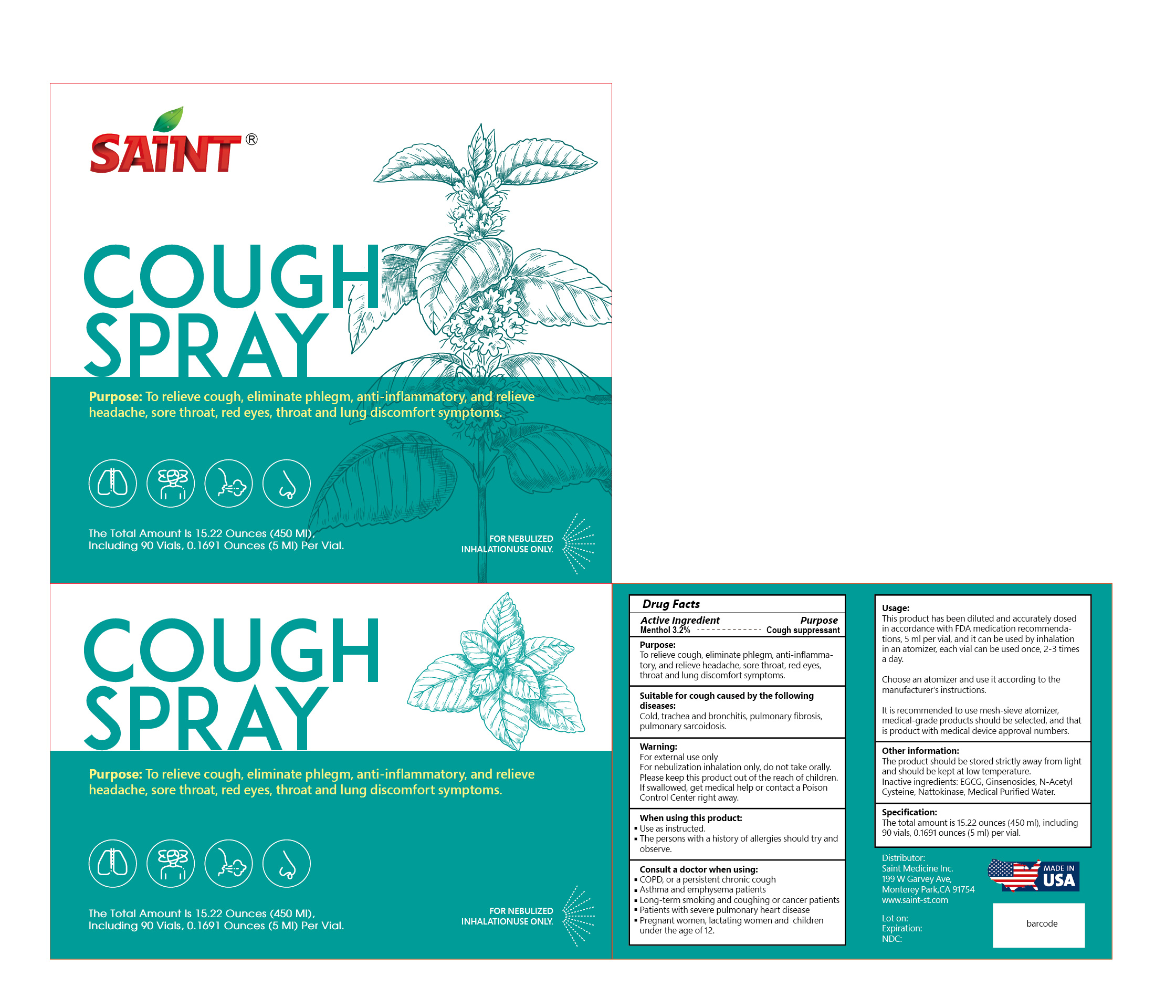 DRUG LABEL: Saint
NDC: 72784-101 | Form: LIQUID
Manufacturer: Saint Medicine, Inc.
Category: otc | Type: HUMAN OTC DRUG LABEL
Date: 20250115

ACTIVE INGREDIENTS: MENTHOL 3.2 g/100 mL
INACTIVE INGREDIENTS: GINSENOSIDES; EPIGALLOCATECHIN GALLATE; ACETYLCYSTEINE; NATTOKINASE; WATER

Saint Cough Spray

Active ingredient

Menthol 3.2%

Purpose

Cough Suppressant

Use

To relieve cough, eliminate phlegm, anti-inflammatory, and relieve headache, sore throat, red eyes, throat and lung discomfort symptoms

Suitable for cough caused by the following diseases:

Cold, trachea and bronchitis, pulmonary fibrosis, pulmonary sarcoidosis

Warnings

For external use only

For nebulization inhalation only, do not take orally.

Please keep this product out of the reach of children.

If swallowed, get medical help or contact a Poison Control Center right away.

KEEP OUT OF REACH OF CHILDREN

Please keep this product out of the reach of children.

Directions

- see important warnings under "When using this product"
- adults & children 2 years & over:
- use 1 tablespoon of solution for each quart of water or 1½ teaspoonful of solution for each pint of water
- add solution directly to cold water only in a hot steam vaporizer (follow manufacturer's directions for using vaporizer)
- breathe in the medicated vapors
- use up to three times daily or as directed by a doctor
- children under 2 years: ask a doctor

When using this product

- Use as instructed.
- The persons with a history of allergies should try and observe.

Counsult a doctor when using:

- COPD, or a persistent chronic cough
- Asthma and emphsema patients
- Long-term smoking and coughing or cancer patients
- Patients with severe pulmonary heart disease
- Pregnant women, lactating women and children under the age of 12.

Usage

This product has been diluted and accurately dosed in accordance with FDA medication recommendations, 5 ml per vial, and it can be used by inhalation in an atomizer, each vial can be used once, 2-3 times a day.

Choose an atomizer and use it according to the manufacturer's instructions.

It is recommended to use mesh-sieve atomizer, medical-grade products should be selected, and that is product with medical device approval numbers.

Other information:

The product should be stored strictly away from light and should be kept at low temperature.

The total amount is 15.22 ounces (150 ml), including 90 vials, 0.1691 ounces (5ml) per vial.

Inactive ingredient

EGCG, Ginsenosides, N-Acetyl Cysteine, Nattokinase, Medical Purified Water

PRINCIPAL DISPLAY PANEL

72784-101-01